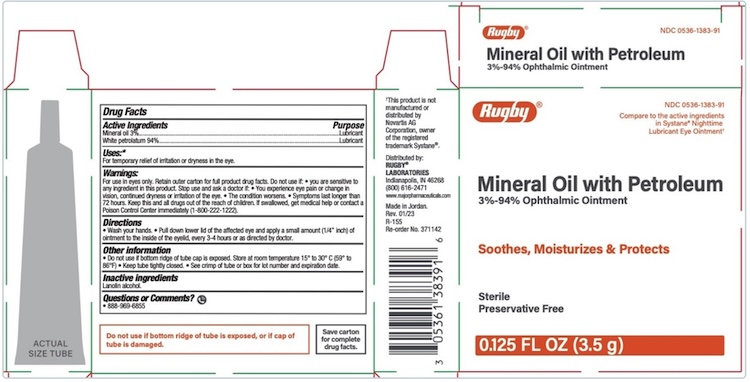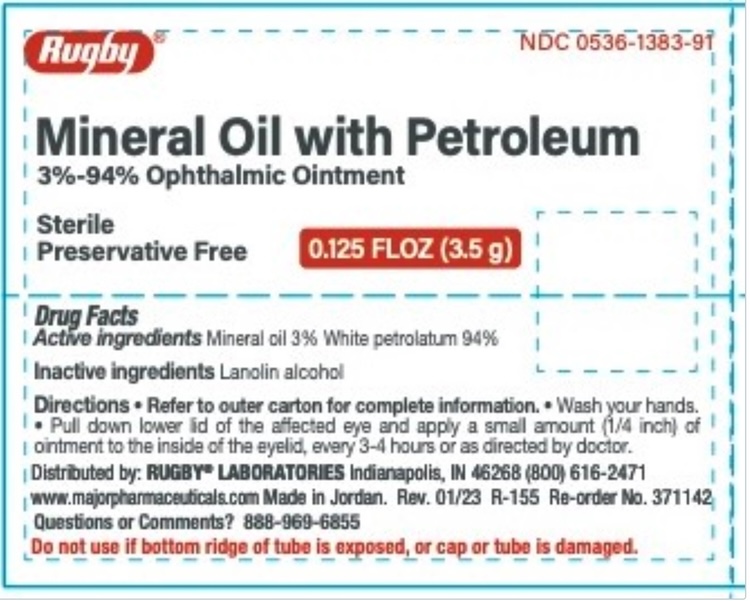 DRUG LABEL: Mineral Oil with Petroleum
NDC: 0536-1383 | Form: OINTMENT
Manufacturer: Rugby Laboratories
Category: otc | Type: HUMAN OTC DRUG LABEL
Date: 20250718

ACTIVE INGREDIENTS: MINERAL OIL 30 mg/1 g; PETROLATUM 940 mg/1 g
INACTIVE INGREDIENTS: LANOLIN

Rugby Mineral Oil with Petroleum

Active ingredients | Purpose
Mineral Oil 3% | Lubricant
White Petrolatum 94% | Lubricant

Uses

- For temporary relief of irritation or dryness in the eye.

Warnings

For use in eyes only. Retain outer carton for full product drug facts.

Do not use if: • you are sensitive to any ingredient in this product.

Do not use if bottom ridge of tube is exposed, or if cap of tube is damaged.

Stop use

Stop use and ask a doctor if you are experiencing any of the following:

• You experience eye pain or change in vision, continued dryness or irritation of the eye. • The condition worsens. • Symptoms last longer than 72 hours

Keep out of reach of children. If swallowed, get medical help or contact a Poison Control Center right away (1-800-222-1222).

Directions

• Wash your hands. • Pull down lower lid of the affected eye and apply a small amount (1/4” inch) of ointment to the inside of the eyelid, every 3-4 hours or as directed by doctor.

Other information

- • Do not use if bottom ridge of tube cap is exposed. Store at room temperature 15° to 30° C (59° to 86°F) • Keep tube tightly closed. • See crimp of tube or box for lot number and expiration date.

Inactive ingredient

Lanolin alcohol.

Questions or Comments? • 888-969-6855